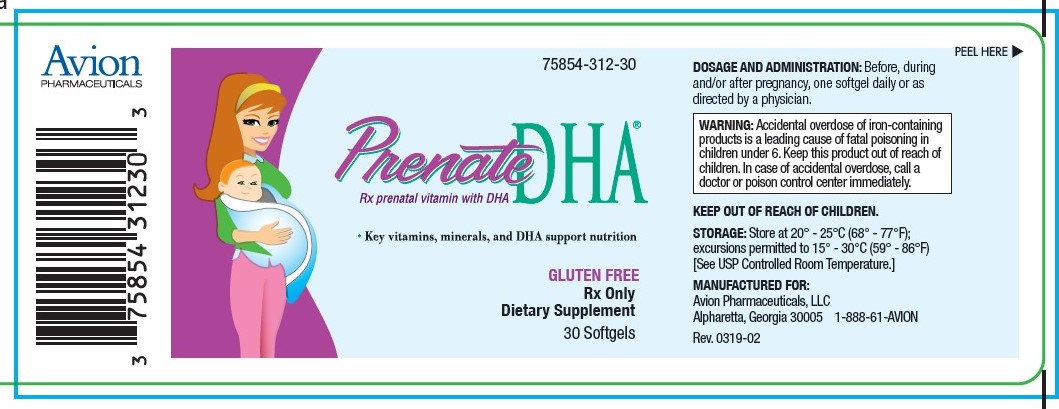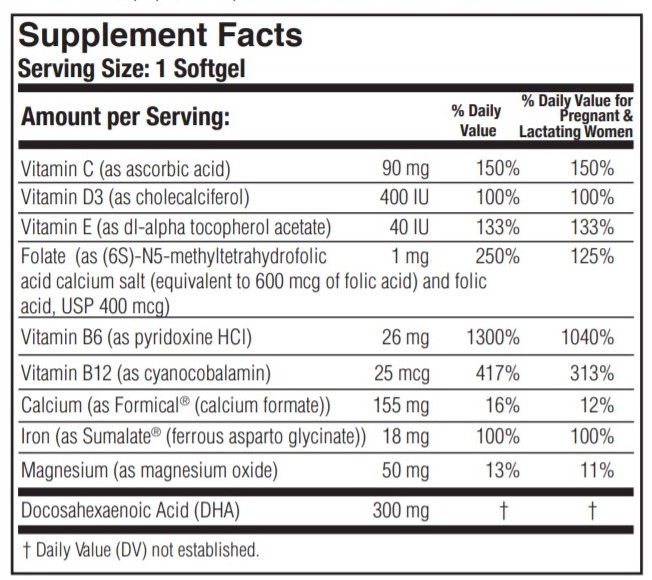 DRUG LABEL: PRENATE DHA
NDC: 75854-312 | Form: CAPSULE, GELATIN COATED
Manufacturer: Avion Pharmaceuticals, LLC
Category: prescription | Type: HUMAN PRESCRIPTION DRUG LABEL
Date: 20240122

ACTIVE INGREDIENTS: ASCORBIC ACID 90 mg/1 1; CHOLECALCIFEROL 400 [iU]/1 1; .ALPHA.-TOCOPHEROL, DL- 40 [iU]/1 1; FOLIC ACID 1 mg/1 1; PYRIDOXINE HYDROCHLORIDE 26 mg/1 1; CYANOCOBALAMIN 25 ug/1 1; CALCIUM FORMATE 155 mg/1 1; FERROUS ASPARTO GLYCINATE 18 mg/1 1; MAGNESIUM OXIDE 50 mg/1 1; DOCONEXENT 300 mg/1 1
INACTIVE INGREDIENTS: GELATIN; GLYCERIN; LECITHIN, SOYBEAN; SOYBEAN OIL; WHITE WAX; WATER; FD&C BLUE NO. 1; TITANIUM DIOXIDE; FD&C RED NO. 3

Prenate DHA®

Rx Only Dietary Supplement

DESCRIPTION

DESCRIPTION: PRENATE DHA® is a prescription prenatal/postnatal multivitamin/mineral/essential fatty acid softgel. Each softgel is blue in color, opaque, and imprinted with “DHA” on one side and blank on the other.

PRENATE DHA® contains fish oil and soy.

INACTIVE INGREDIENT

OTHER INGREDIENTS: Gelatin capsule (FD&C Blue #1, FD&C Red #3, gelatin, glycerin, purified water, sorbitol and titanium dioxide), soybean oil, soy lecithin, and white beeswax.

INDICATIONS AND USAGE

INDICATIONS: PRENATE DHA® is a multivitamin/multimineral fatty acid dietary supplement indicated for use in improving the nutritional status of women throughout pregnancy and in the postnatal period for both lactating and nonlactating mothers. PRENATE DHA® can also be beneficial in improving the nutritional status of women prior to conception.

CONTRAINDICATIONS

CONTRAINDICATIONS: PRENATE DHA® is contraindicated in patients with a known hypersensitivity to any of the ingredients.

WARNINGS

WARNING: Ingestion of more than 3 grams of omega-3 fatty acids (such as DHA) per day has been shown to have potential antithrombotic effects, including an increased bleeding time and International Normalized Ratio (INR). Administration of omega-3 fatty acids should be avoided in patients taking anticoagulants and in those known to have an inherited or acquired predisposition to bleeding.

PRECAUTIONS

PRECAUTIONS: Folic acid alone is improper therapy in the treatment of pernicious anemia and other megaloblastic anemias where Vitamin B12 is deficient. Folic acid in doses above 1.0 mg daily may obscure pernicious anemia in that hematologic remission can occur while neurological manifestations progress.

BOXED WARNING

WARNING: Accidental overdose of iron-containing products is a leading cause of fatal poisoning in children under 6. Keep this product out of reach of children. In case of accidental overdose, call a doctor or poison control center immediately.

ADVERSE REACTIONS

ADVERSE REACTIONS: Allergic sensitization has been reported following both oral and parenteral administration of folic acid.

DOSAGE AND ADMINISTRATION: Before, during and/or after pregnancy, one softgel daily or as directed by a physician.

HOW SUPPLIED

HOW SUPPLIED: Bottles of 30 softgels (75854-312-30).

The listed product number is not a National Drug Code. Instead, Avion Pharmaceuticals has assigned a product code formatted according to standard industry practice to meet the formatting requirements of pharmacy and healthcare insurance computer systems.

STORAGE AND HANDLING

Store at 20° - 25°C (68° - 77°F); excursions permitted to 15° - 30°C (59° - 86°F) [See USP Controlled Room Temperature.]

MANUFACTURED FOR:
Avion Pharmaceuticals, LLC
Alpharetta, Georgia 30005
1-888-61-AVION

Formical® is a registered trademark of Nephro-Tech 1, LLC, covered by one or more claims of U.S. Patent No. 6,528,542.

Sumalate® is a registered trademark of Albion Laboratories, Inc., covered by one or more claims of U.S. Patent Nos. 5,516,925, 6,716,814, 8,007,846, and 8,425,956.

PRENATE® is a registered trademark of Avion Pharmaceuticals, LLC. Under license from Avion Pharmaceuticals, LLC.

All rights reserved.

Rev. 0519-02

PACKAGE LABEL.PRINCIPAL DISPLAY PANEL

75854-312-30

Prenate DHA®

Rx prenatal vitamin & DHA

- Key vitamins, minerals, and DHA support nutrition

GLUTEN FREE
Rx Only
Dietary Supplement

30 Softgels